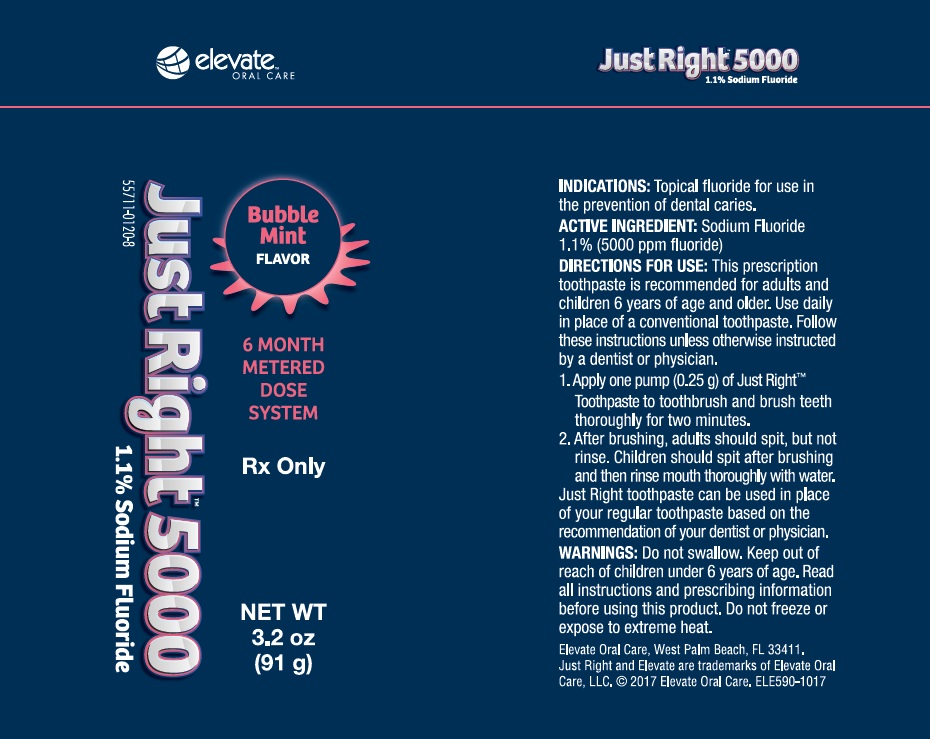 DRUG LABEL: Just Right 5000
NDC: 57511-0120 | Form: GEL, DENTIFRICE
Manufacturer: Elevate Oral Care
Category: otc | Type: HUMAN OTC DRUG LABEL
Date: 20180207

ACTIVE INGREDIENTS: SODIUM FLUORIDE 1.1 g/100 g
INACTIVE INGREDIENTS: WATER; SORBITOL; HYDRATED SILICA; GLYCERIN; FD&C BLUE NO. 1; SACCHARIN; POTASSIUM PHOSPHATE, MONOBASIC; XANTHAN GUM

Just Right 5000 - Bubble Mint

OTC - ACTIVE INGREDIENT SECTION

Sodium Fluoride 1.1% Anticavity toothpaste

INDICATIONS & USAGE SECTION

helps protect against cavities

WARNINGS SECTION

Keep out of reach of children under 6 years of age: if more than used for brushing is accidentally swallowed, get medical help or contact a poison control center right away.

OTC - KEEP OUT OF REACH OF CHILDREN SECTION

Keep out of reach of children under 6 years of age:

INSTRUCTIONS FOR USE SECTION

Directions: *adults and children 2 years and older: wet a toothbrush and pump once to apply a pea-sized (~0.25 gram) amount of toothpaste onto a toothbrush * brush thoroughly after meals or at least twice a day or use as directed by a dentist or physician. * to minimize swallowing, only pump once to dispense a pea-sized amount for children under 6 years. * supervise children's brushing untill good habits are established. * children under 2 years: ask dentist or physician.

INACTIVE INGREDIENT SECTION

Inactive ingredients; Sorbitol, Water, Glycerin, Hydrated silica, PEG-8, Bubble Gum/Mint Flavor, Sodium Lauryl Sulfate, Xanthan Gum, Potassium Phosphate, Sodium Benzoate, Sodium Saccharin, Mica, Blue 1.1% Solution

OTC - QUESTIONS SECTION

Questions? 1-877-866-9113 or visit our website at www.elevateoralcare.com

OTC - PURPOSE SECTION

Helps protect against Cavities

DOSAGE & ADMINISTRATION SECTION

Directions: *adults and children 2 years and older: wet a toothbrush and pump once to apply a pea-sized (~0.25 gram) amount of toothpaste onto a toothbrush * brush thoroughly after meals or at least twice a day or use as directed by a dentist or physician. * to minimize swallowing, only pump once to dispense a pea-sized amount for children under 6 years. * supervise children's brushing untill good habits are established. * children under 2 years: ask dentist or physician.